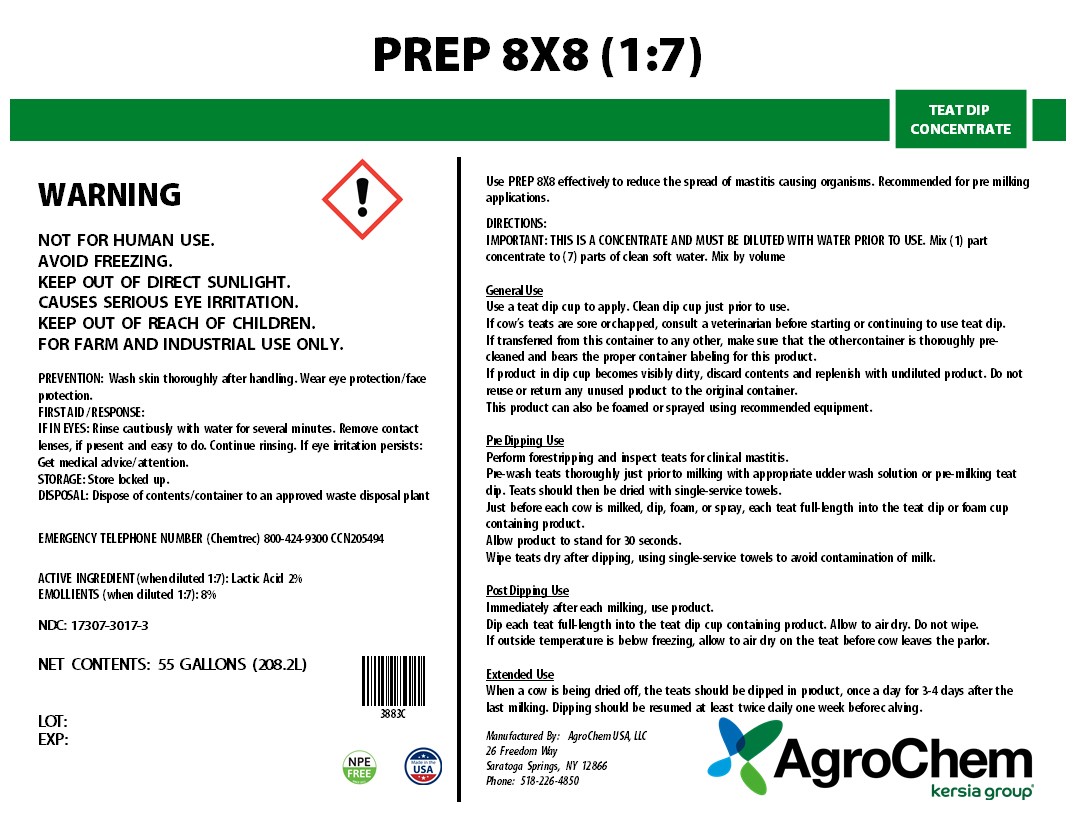 DRUG LABEL: PREP 8X8
NDC: 17307-3017 | Form: SOLUTION
Manufacturer: AgroChem USA, LLC.
Category: animal | Type: OTC ANIMAL DRUG LABEL
Date: 20241106

ACTIVE INGREDIENTS: LACTIC ACID 0.184 kg/1 kg
INACTIVE INGREDIENTS: WATER; DODECYLBENZENESULFONIC ACID; Glycerin; FD&C YELLOW NO. 6

PREP 8X8

PREP 8X8

TEAT DIP CONCENTRATE

WARNING

KEEP OUT OF REACH OF CHILDREN

WARNINGS AND PRECAUTIONS

NOT FOR HUMAN USE.

AVOID FREEZING.

KEEP OUT OF DIRECT SUNLIGHT.

CAUSES SERIOUS EYE IRRITATION.

FOR FARM AND INDUSTRIAL USE ONLY.

PREVENTION: Wash skin thoroughly after handling. Wear eye protection/ face protection.

FIRST AID / RESPONSE:

IF IN EYES: Rinse cautiously with water for several minutes. Remove contact lenses, if present and easy to do. Continue rinsing. If eye irritation persists: Get medical advice/ attention.

STORAGE: Store locked up.

DISPOSAL: Dispose of contents/ container to an approved waste disposal plant

EMERGENCY TELEPHONE NUMBER (Chemtrec) 800-424-9300 CCN205494

NDC: 17307-3017-3

NET CONTENTS: 55 GALLON (208.2L)

LOT:

EXP. DATE:

ACTIVE INGREDIENT (when diluted 1:7): Lactic Acid 2%

INACTIVE INGREDIENT

EMOLLIENTS (when diluted 1:7): 8%

Use PREP 8X8 CONCENTRATE effectively to reduce the spread of mastitis causing organisms. Recommended for pre milking applications.

DIRECTIONS:

IMPORTANT: THIS IS A CONCENTRATE AND MUST BE DILUTED WITH WATER PRIOR TO USE. Mix (1) part concentrate to (7) parts of clean, soft water. Mix by volume

General Use

Use a teat dip cup to apply. Clean dip cup just prior to use.

If cow’s teats are sore or chapped, consult a veterinarian before starting or continuing to use teat dip.

If transferred from this container to any other, make sure that the other container is thoroughly pre-cleaned and bears the proper container labeling for this product.

If product in dip cup becomes visibly dirty, discard contents and replenish with undiluted product. Do not reuse or return any unused product to the original container.

This product can also be foamed or sprayed using recommended equipment.

Pre Dipping Use

Perform forestripping and inspect teats for clinical mastitis.

Pre-wash teats thoroughly just prior to milking with appropriate udder wash solution or pre-milking teat dip. Teats should then be dried with single-service towels.

Just before each cow is milked, dip, foam, or spray, each teat full-length into the teat dip or foam cup containing product.

Allow product to stand for 30 seconds.

Wipe teats dry after dipping, using single-service towels to avoid contamination of milk.

Post Dipping Use

Immediately after each milking, use product.

Dip each teat full-length into the teat dip cup containing product. Allow to air dry. Do not wipe.

If outside temperature is below freezing, allow to air dry on the teat before cow leaves the parlor.

Extended Use

When a cow is being dried off, the teats should be dipped in product, once a day for 3-4 days after the last milking. Dipping should be resumed at least twice daily one week before

calving.

Manufactured By:

AgroChem USA, LLC 26 Freedom Way • Saratoga Springs, NY 12866 • (518)226-4850